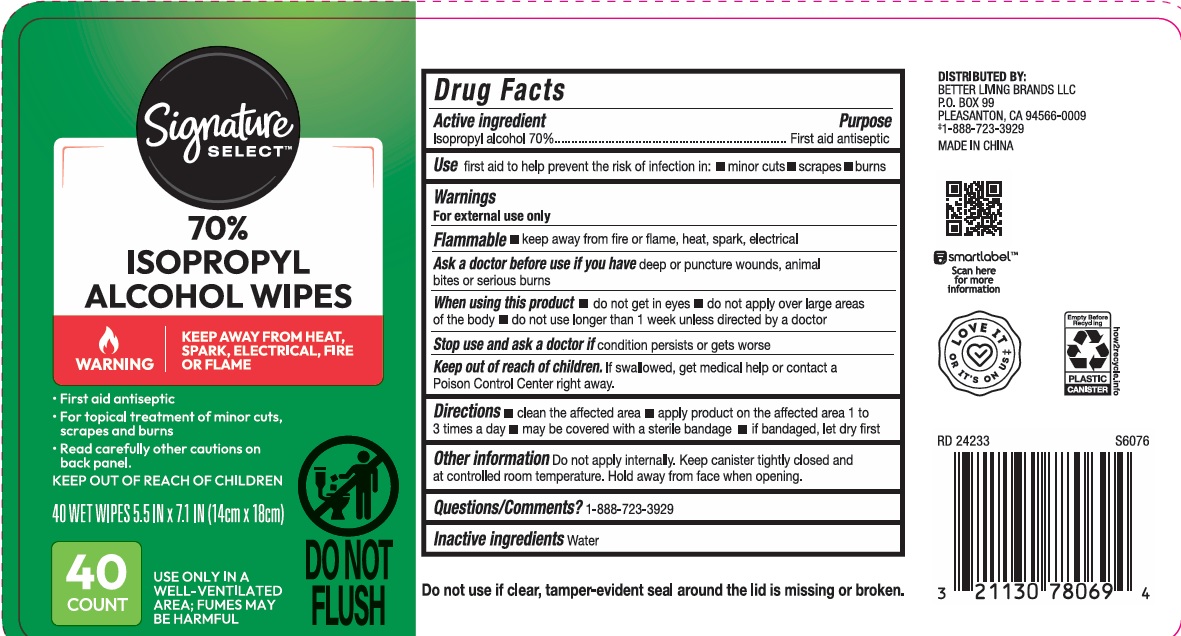 DRUG LABEL: Signature Select isopropyl alcohol wipes
NDC: 74149-114 | Form: SWAB
Manufacturer: Yiwu Yangjie Daily Chemicals Co.,Ltd.
Category: otc | Type: HUMAN OTC DRUG LABEL
Date: 20250704

ACTIVE INGREDIENTS: ALCOHOL 70 g/100 g
INACTIVE INGREDIENTS: WATER

ISOPROPYL Alcohol Wipes

Active Ingredient

Ispropyl Alcohol 70%，

Purpose

first aid Antiseptic

USE

first aid to help prevent the risk of infection in：minor cuts; scrapes; burns

Warning

- For external use only.
- Flammable, keep away from fire or flame.

When using this product

- do not get in eyes.
- do not apply over largge areas of the body
- do not use longer than 1 week unless directed by a doctor.

Other Information:

Do not apply internally. keep canister tightly closed and at controlled room teperature. Hold aeay from face when opening.

KEEP OUT OF REACH OF CHILDREN

●If swallowed, get medical help or contact a Poison Contrl Center right away.

Directions

- clean the affected area
- apply product on the affected area 1 to 3 times a day
- may be covered with a sterile bandage
- if bandaged, let dry first

Inactive ingredients

water